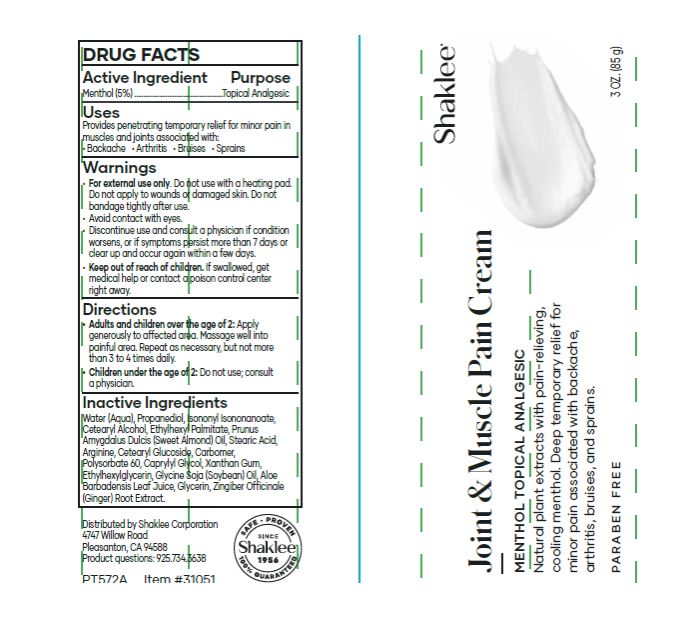 DRUG LABEL: Joint and Muscle Pain
NDC: 59899-022 | Form: CREAM
Manufacturer: Shaklee Corporation
Category: otc | Type: HUMAN OTC DRUG LABEL
Date: 20240130

ACTIVE INGREDIENTS: MENTHOL 50 mg/1 g
INACTIVE INGREDIENTS: WATER; PROPANEDIOL; ISONONYL ISONONANOATE; CETOSTEARYL ALCOHOL; ETHYLHEXYL PALMITATE; ALMOND OIL; PHENOXYETHANOL; STEARIC ACID; ARGININE; CETEARYL GLUCOSIDE; CARBOMER HOMOPOLYMER, UNSPECIFIED TYPE; POLYSORBATE 60; CAPRYLYL GLYCOL; XANTHAN GUM; TOCOPHEROL; ETHYLHEXYLGLYCERIN; ALOE VERA LEAF; GLYCERIN; GINGER

Joint & Muscle Pain Cream

Active Ingredient

Menthol (5%)

Purpose

Topical Analgesic

Uses

Provides penetrating temporary relief for minor pain in muscles and joints associated with:

- Backache
- Arthritis
- Bruises
- Sprains

Warnings

For external use only.

Do not use

- with a heating pad. Do not apply to wounds or damaged skin. Do not bandage tightly after use.
- Avoid contact with eyes.
- Discontinue use and consult a physician if condition worsens, or if symptoms persist more than 7 days or clear up and occur again within a few days.

Keep out of reach of children.

If swallowed, get medical help or contact a poison control center right away.

Directions

Apply generously to affected area. Massage well into painful area. Repeat as necessary, but not more than 3 to 4 times daily. Adults and children over the age of 2:

Do not use; consult a physician. Children under the age of 2:

Inactive Ingredients

Water, Propanediol, Isononyl Isononanoate, Cetearyl Alcohol, Ethylhexyl Palmitate, Prunus Amygdalus Dulcis (Sweet Almond) Oil 1%, Phenoxyethanol, Stearic Acid, Arginine, Cetearyl Glucoside, Carbomer, Polysorbate 60, Caprylyl Glycol, Xanthan Gum, Tocopherol, Ethylhexylglycerin, Aloe Barbadensis Leaf Juice, Glycerin, Zingiber Officinale (Ginger) Root Extract.